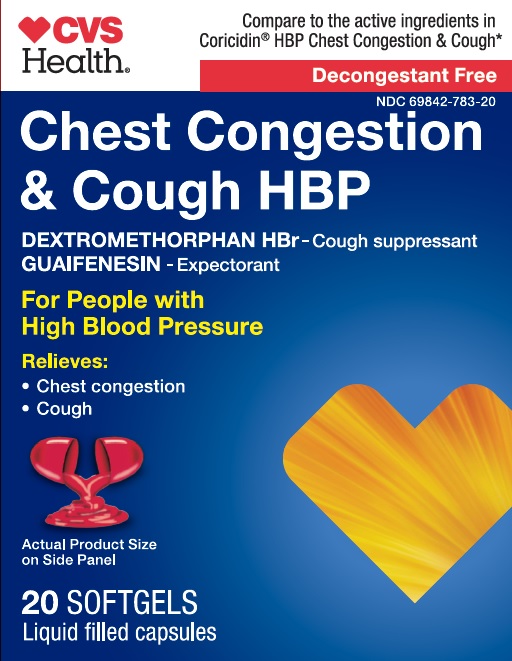 DRUG LABEL: MAXIMUM STRENGTH CHEST CONGESTION AND COUGH
NDC: 69842-783 | Form: CAPSULE, GELATIN COATED
Manufacturer: CVS PHARMACY, INC.
Category: otc | Type: HUMAN OTC DRUG LABEL
Date: 20241218

ACTIVE INGREDIENTS: DEXTROMETHORPHAN HYDROBROMIDE 10 mg/1 1; GUAIFENESIN 200 mg/1 1
INACTIVE INGREDIENTS: FD&C RED NO. 40; GELATIN; GLYCERIN; POLYETHYLENE GLYCOL 400; POVIDONE K30; PROPYLENE GLYCOL; WATER; SORBITOL; TITANIUM DIOXIDE

Chest Congestion & Cough HBP

Drug Facts

ACTIVE INGREDIENT

PURPOSE

Active ingredients (in each softgel) | Purposes
Dextromethorphan HBr, USP 10 mg | Cough suppressant
Guaifenesin, USP 200 mg | Expectorant

Uses

- temporarily relieves cough due to minor throat and bronchial irritation as may occur with a cold
- helps loosen phlegm (mucus) and thin bronchial secretions to drain bronchial tubes

Warnings

Do not use if you are now taking a prescription monoamine oxidase inhibitor (MAOI) (certain drugs for depression, psychiatric, or emotional conditions, or Parkinson's disease), or for 2 weeks after stopping the MAOI drug. If you do not know if your prescription drug contains an MAOI, ask a doctor or pharmacist before taking this product.

Ask a doctor before use if you have

- cough that occurs with too much phlegm (mucus)
- cough that lasts or is chronic such as occurs with smoking, asthma, chronic bronchitis, or emphysema

Stop use and ask a doctor if cough lasts more than 7 days, comes back, or is accompanied by fever, rash, or persistent headache. These could be signs of a serious condition.

PREGNANCY OR BREAST FEEDING

If pregnant or breast-feeding, ask a health professional before use.

Keep out of reach of children. In case of overdose, get medical help or contact a Poison Control Center right away.

Directions

- do not take more than 12 softgels in any 24-hour period
- this adult product is not intended for use in children under 12 years of age

age | dose
adults and children 12 years and over | 2 softgels every 4 hours
children under 12 years | do not use

Other information

- store at 20-25°C (68-77°F).
- avoid excessive heat above 40°C (104°F).

Inactive ingredients

FD&C Red-40, gelatin, glycerin, polyethylene glycol, povidone, propylene glycol, purified water, special sorbitol, titanium dioxide

Questions or comments?

1-888-333-9792

PRINCIPAL DISPLAY PANEL

Compare to the active ingredients in Robitussin® Maximum

Strength Cough+Chest Congestion DM*

Maximum Strength

Cough + Chest Congestion DM

DEXTROMETHORPHAN HBr / COUGH SUPPRESSANT
GUAIFENESIN/ EXPECTORANT

MAXIMUM STRENGTH

Relieves

cough
chest congestion
20 SOFTGELS